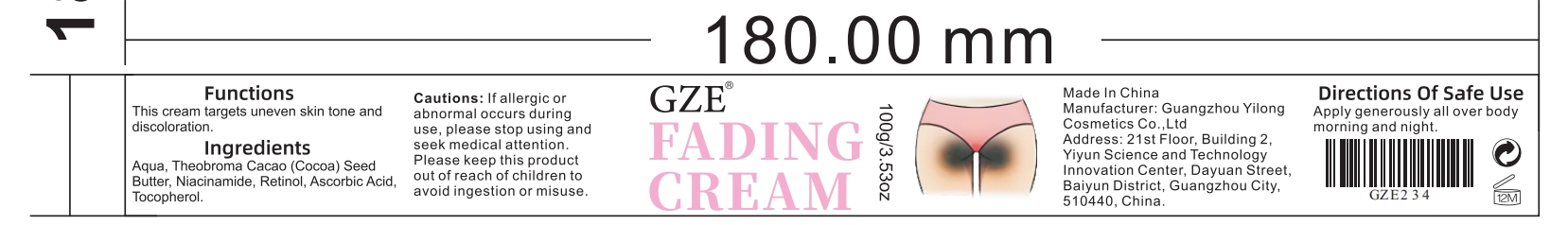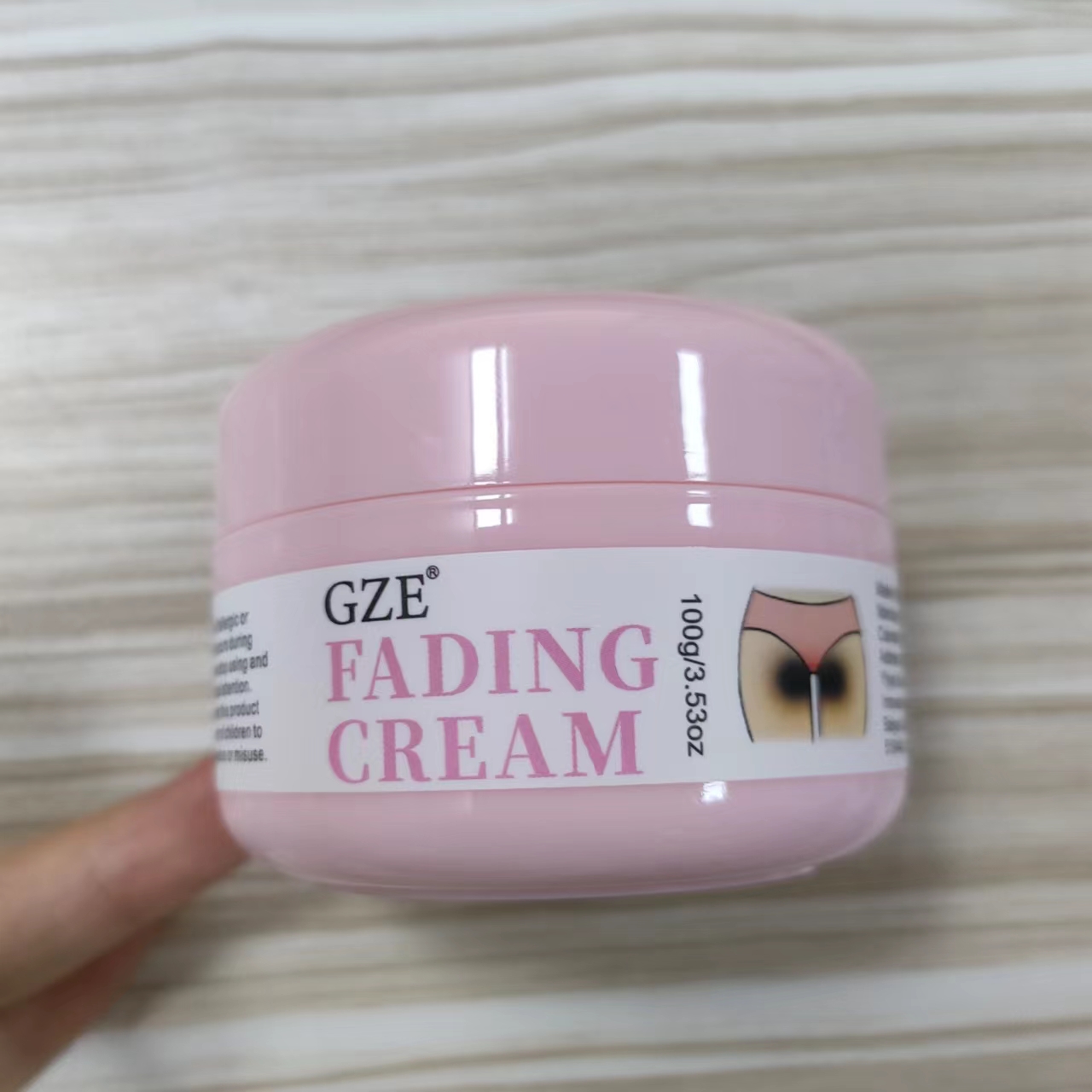 DRUG LABEL: GZE Fading Cream
NDC: 83566-234 | Form: CREAM
Manufacturer: Guangzhou Yilong Cosmetics Co., Ltd
Category: otc | Type: HUMAN OTC DRUG LABEL
Date: 20240820

ACTIVE INGREDIENTS: ASCORBIC ACID 2 g/100 g; NIACINAMIDE 4.51 g/100 g; RETINOL 1 g/100 g
INACTIVE INGREDIENTS: COCOA BUTTER; TOCOPHEROL; WATER

GZE Fading Cream

ACTIVE INGREDIENT

Niacinamide 4.51%

Retinol 2%

Ascorbic Acid 1%

INACTIVE INGREDIENT

Aqua

Theobroma Cacao (Cocoa) Seed Butter

Tocopherol

INDICATIONS AND USAGE

Apply generously all over body morning and night.

PURPOSE

Skin whitening.

WARNINGS

For external use only.

Stop use and ask a doctor if rash occurs.

Do not use on damaged or broken skin

When using this product keep out of eyes. Rinse with water to remove.

Keep out of reach of children. If swallowed, get medical help or contact a Poison Control Center right away.

DOSAGE AND ADMINISTRATION

Apply generously all over body morning and night.